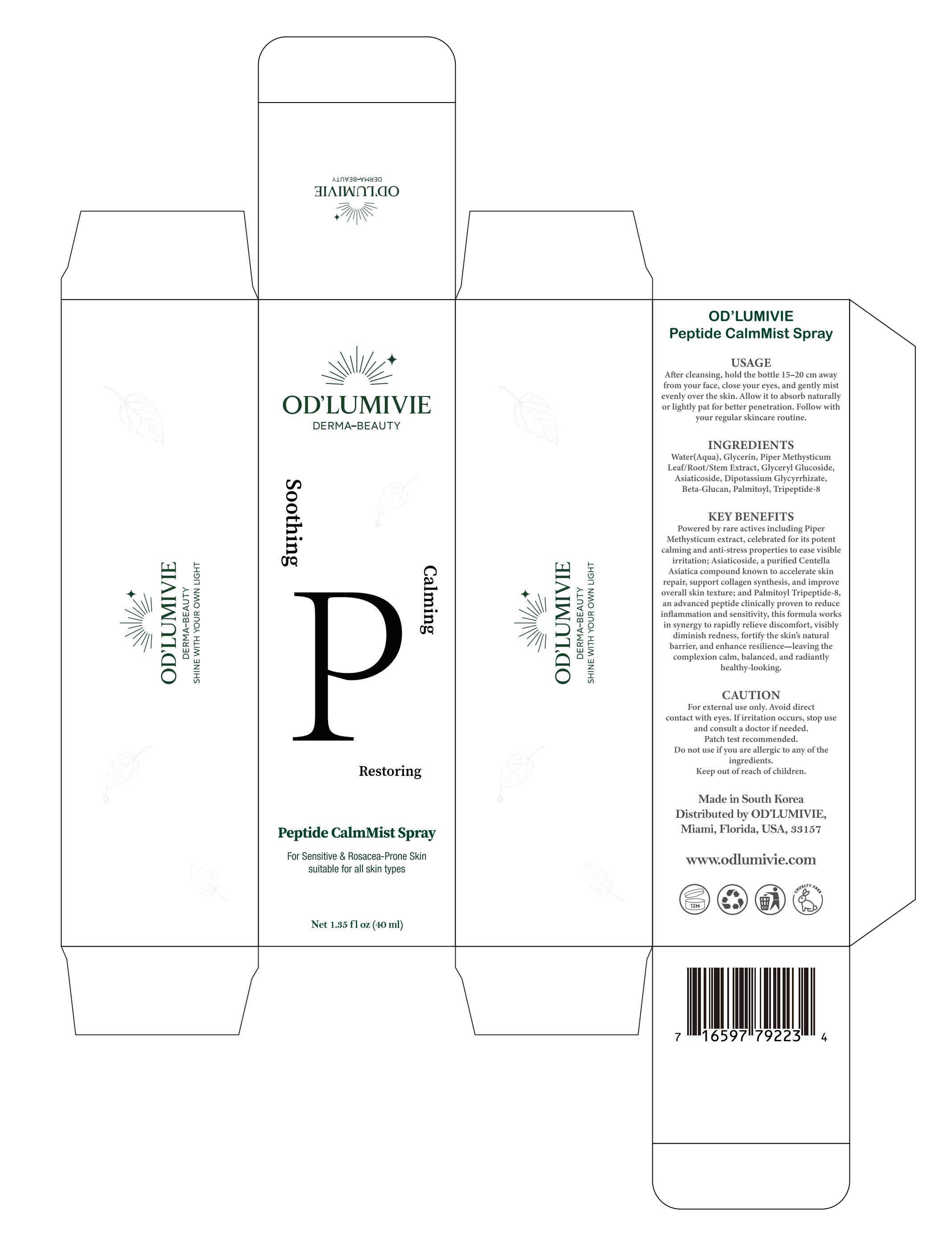 DRUG LABEL: ODLUMIVIE Peptide CalmMist
NDC: 87036-027 | Form: SPRAY
Manufacturer: OD’LUMIVIE
Category: otc | Type: HUMAN OTC DRUG LABEL
Date: 20251111

ACTIVE INGREDIENTS: PALMITOYL TRIPEPTIDE-8 1 g/100 mL
INACTIVE INGREDIENTS: WATER; PIPER METHYSTICUM WHOLE; GLYCERIN; GLYCERYL GLUCOSIDE; ASIATICOSIDE; DIPOTASSIUM GLYCYRRHIZATE

ACTIVE INGREDIENT

INACTIVE INGREDIENT

Water(Aqua), Tremella fuciformis extract, glycerin, Dendrobium ofcinale stemextract, calcium gluconate, beta glucan

PURPOSE

KEY BENEFITSPowered by rare actives including PiperMethysticum extract, celebrated for its potentcalming and anti-stress properties to ease visibleirritation; Asiaticoside, a purifed CentellaAsiatica compound known to accelerate skinrepair, support collagen synthesis, and improveoverall skin texture; and Palmitoyl Tripeptide-8,an advanced peptide clinically proven to reduceinflammation and sensitivity, this formula worksin synergy to rapidly relieve discomfort, visiblydiminish redness, fortify the skin's naturalbarrier, and enhance resilience-leaving thecomplexion calm, balanced, and radiantlyhealthy-looking

WARNINGS

CAUTION
For external use only. Avoid directcontact with eyes. Ifirritation occurs, stop useand consult a doctor if needed.Patch test recommended.Do not use if you are allergic to any of theingredients.Keep out of reach of children.

DO NOT USE

CAUTION
For external use only, Avoid direct contact with eyes. Ifirritation occurs, stop useand consult a doctor if needed. Patch test recommended, Do not use if you areallergic to any of the ingredients. Keep out of reach of children.

KEEP OUT OF REACH OF CHILDREN

CAUTION
For external use only, Avoid direct contact with eyes. Ifirritation occurs, stop useand consult a doctor if needed. Patch test recommended, Do not use if you areallergic to any of the ingredients. Keep out of reach of children.

STOP USE

CAUTION
For external use only, Avoid direct contact with eyes. Ifirritation occurs, stop useand consult a doctor if needed. Patch test recommended, Do not use if you areallergic to any of the ingredients. Keep out of reach of children.

USAGE
After cleansing, hold the bottle 15-20 cm awayfrom your face, close your eyes, and gently mistevenly over the skin. Allow it to absorb naturallyor lightly pat for better penetration. Follow withyour regular skincare routine.

WHEN USING

USAGE
After cleansing, hold the bottle 15-20 cm awayfrom your face, close your eyes, and gently mistevenly over the skin. Allow it to absorb naturallyor lightly pat for better penetration. Follow withyour regular skincare routine.

DOSAGE AND ADMINISTRATION

USAGE
After cleansing, hold the bottle 15-20 cm awayfrom your face, close your eyes, and gently mistevenly over the skin. Allow it to absorb naturallyor lightly pat for better penetration. Follow withyour regular skincare routine.

PACKAGE LABEL

ODLUMIVIE
DERMA-BEAUTY
Soothing
Calming
HIAIWAT.QO
LHSI NMO NOA HLIM INIHS
ALny38-yW830
USAGE
After cleansing, hold the bottle 15-20 cm awayfrom your face, close your eyes, and gently misevenly over the skin. Allow it to absorb naturallor lightly pat for better penetration. Follow wit!your regular skincare routine.
INGREDIENTS
Water(Aqua),Glycerin, Piper MethysticumLeaf/Root/Stem Extract, Glyceryl GlucosideAsiaticoside, Dipotassium Glycyrrhizate,Beta-Glucan, Palmitoyl, Tripeptide-8
KEY BENEFITS
Powered py rare actives including PiperMethysticum extract,celebrated for its potentcalming and anti-stress properties to ease visiblirritation:Asiaticoside,a purifed CentellaAsiatica compound known to accelerate skinrepair, support collagen synthesis, and improvoverall skin texture: and Palmitoyl Tripeptide-8an advanced peptide clinically proven to reducinfammation and sensitivity, this formula workin synergy to rapidly relieve discomfort, visiblydiminish redness, fortify the skin's naturalbarrier, and enhance resilience-leaving thecomplexion calm,balanced, and radiantly
healthy-looking.
CAUTIONFor external use only, Avoid directcontact with eyes. Ifirritation occurs, stop useand consult a doctor ifneeded.Patch test recommended.Do not use ifyou are allergic to any of the
Restoring
Peptide CalmMist Spray
For Sensitive & Rosacea-Prone Skinsuitable for all skin types
ingredients.
Keep out ofreach ofchildren.
Made in South KoreaDistributed by ODTUMIVIEMiami, Florida,USA,33157
wwwodlumivie.com